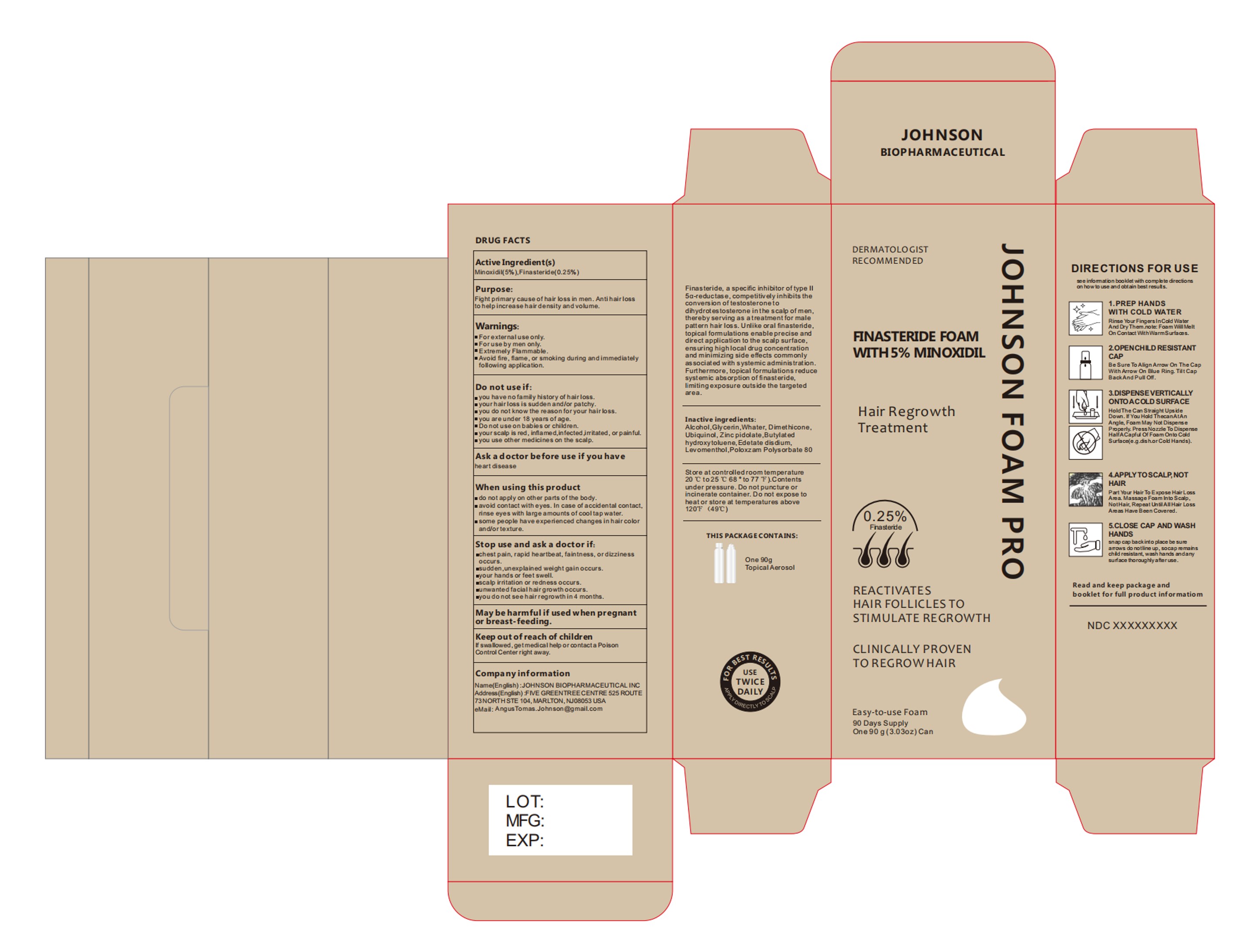 DRUG LABEL: JOHNSON FOAM PRO
NDC: 84539-002 | Form: AEROSOL, FOAM
Manufacturer: JOHNSON BIOPHARMACEUTICAL INC.
Category: otc | Type: HUMAN OTC DRUG LABEL
Date: 20250611

ACTIVE INGREDIENTS: FINASTERIDE 0.25 g/100 g; MINOXIDIL 5 g/100 g
INACTIVE INGREDIENTS: ALCOHOL; POLOXAMER 407; ZINC PIDOLATE; GLYCERIN; EDETATE DISODIUM; CETYL PEG/PPG-10/1 DIMETHICONE (HLB 5); BUTYLATED HYDROXYTOLUENE; WATER; LEVOMENTHOL; UBIQUINOL; POLYSORBATE 80

JOHNSON FOAM PRO

JOHNSON FOAM PRO

ACTIVE INGREDIENT

MINOXIDIL 5%
FINASTERIDE 0.25%

PURPOSE

Fight primarycause ofhalr loss in men.Antihalrlosstohelpincreasehairdenslty andvolume.

INDICATIONS AND USAGE

Fight primarycause ofhalr loss in men.Antihalrlosstohelpincreasehairdenslty andvolume.

WARNINGS

Forexternaluse only.
Foruse by men only.
Extremely Flammable.
Avoid fire, flame, or smoking during andimmedlately following application.

DO NOT USE

you have no famlly hlstory of halrloss.
you rhalrloss is sudden and/or patchy.
you do not know the reason for your halr loss.
you are under 18 years of age.
Do not useonbables or chikdren.
yourscalp is red, inflamed,infected,rritated, or painful.
you use other medicines on the scalp.

WHEN USING

do not apply on other parts of the body.
avold contact with eyes. In case ofaccldental contact.rinse eyes with large amounts ofcooltap water.
some people have experienced changes in halr colorandortexture.

STOP USE

chest pain, rapld heartbeat, faintness,ordlzziness occurs.
sudden,unexplained weight gain occurs.
your hands or feet swell.
scalp irritation or redness occurs.
umwanted facialhalrgrowth occurs.
you donot see halrregrowthin 4 months.

KEEP OUT OF REACH OF CHILDREN

If swallowed,getmedical help or contacta Poison
Control Center right away.

DOSAGE AND ADMINISTRATION

1.PREP HANDSWITH COLD WATERRinse Your Fingers inCald WaterAnd Doy Them note: Foam Wll MeltOn Contat WithWarmSurfacs.
2.OPENCHILD RESISTANTCAPBe Sure To Align Arrow On The CapWith Arrow On Blue Ring.Tit capBadkAnd Pull ot.
3.DISPENSEVERTICALLYONTOACOLDSURFACEHoldThe Can Staght UpsideDown.if You Hdd ThecanAtAnAngle, Foam May Nat DispansePoperhy, PressNozzie To Dispe nseHalfACapiu OfFoam Onto CaldSuface(e gdshorCod Hands).
4.APPLYTOSCALP, NOTHAIRPart Your Hair To Expose HairLossAra. Massage Foamhno Sedp.NotHair, Repeat UnslAllHar LossAras Have Been Covered.
5.CLOSE CAP AND WASHHANDSsn ap cap back into plaoe be surearows do notline up,socapmmanschid resistant, wash hands andamysurace thoroughly a feruse .

INACTIVE INGREDIENT

ALCOHOL
GLYCERIN
WHATER
CETYL PEG/PPG-10/1 DIMETHICONE (HLB 5)
UBIQUINOL
ZINC PIDOLATE
BUTYLATED HYDROXYTOLUENE
EDETATE DISODIUM
LEVOMENTHOL
Poloxzam
POLYSORBATE 80